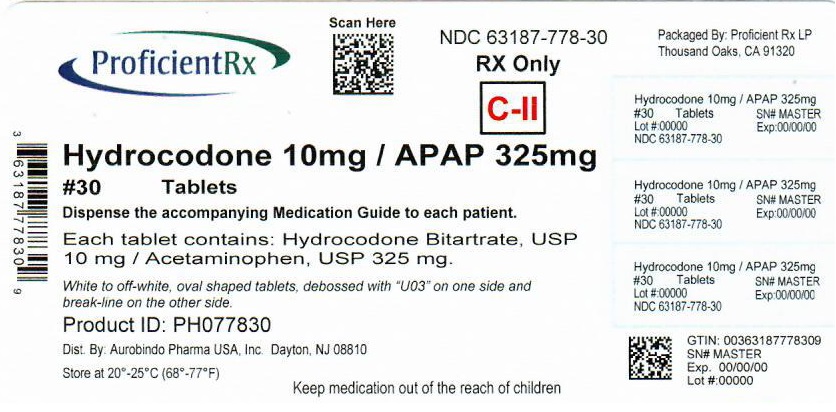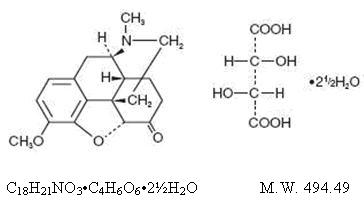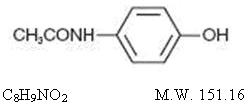 DRUG LABEL: Hydrocodone Bitartrate and Acetaminophen
NDC: 63187-778 | Form: TABLET
Manufacturer: Proficient Rx LP
Category: prescription | Type: HUMAN PRESCRIPTION DRUG LABEL
Date: 20220401
DEA Schedule: CII

ACTIVE INGREDIENTS: HYDROCODONE BITARTRATE 10 mg/1 1; ACETAMINOPHEN 325 mg/1 1
INACTIVE INGREDIENTS: SILICON DIOXIDE; CROSCARMELLOSE SODIUM; CROSPOVIDONE (120 .MU.M); MAGNESIUM STEARATE; MICROCRYSTALLINE CELLULOSE; POVIDONE K30; STARCH, CORN; STEARIC ACID

Hydrocodone Bitartrate and Acetaminophen Tablets, USP

WARNING

WARNING:ADDICTION, ABUSE, AND MISUSE; LIFE-THREATENING RESPIRATORY DEPRESSION;ACCIDENTAL INGESTION; NEONATAL OPIOID; WITHDRAWAL SYNDROME; and HEPATOTOXICITY

Addiction, Abuse, and Misuse

Hydrocodone bitartrate and acetaminophen tablets exposes patients and other users to the risks of opioid addiction, abuse, and misuse, which can lead to overdose and death. Assess each patient’srisk prior to prescribing hydrocodone bitartrate and acetaminophen tablets, andmonitor all patients regularly for the development of these behaviors orconditions [see WARNINGS].

Life-ThreateningRespiratory Depression

Serious, life-threatening, or fatal respiratory depression may occur with use of hydrocodone bitartrate and acetaminophen tablets. Monitor for respiratory depression, especially during initiation of hydrocodone bitartrate and acetaminophen tablets or following adose increase [see WARNINGS].

Accidental Ingestion

Accidental ingestion of even one dose of hydrocodone bitartrate and acetaminophen tablets, especially by children, can result in a fatal overdose of Hydrocodone bitartrate and acetaminophen tablets[see WARNINGS].

Neonatal Opioid Withdrawal Syndrome

Prolonged use of hydrocodone bitartrate and acetaminophen tablets during pregnancy can result in neonatal opioid withdrawal syndrome, which may be life-threatening if not recognized andtreated, and requires management according to protocols developed by neonatology experts. If opioid use is required for a prolonged period in apregnant woman, advise the patient of the risk of neonatal opioid withdrawal syndrome and ensure that appropriate treatment will be available [seeWARNINGS].

Hepatotoxicity

Acetaminophenhas been associated with cases of acute liver failure, at times resulting inliver transplant and death. Most of the cases of liver injury are associatedwith the use of acetaminophen at doses that exceed 4,000 milligrams per day,and often involve more than one acetaminophen-containing product (seeWARNINGS).

Risks from concomitant use with Benzodiazepines or other CNS Depressants

Concomitant use of opiods with benzodiazepines or other central nervous system (CNS) depressants including alcohol, may result in profound sedation, respiratory depression, coma, and death. [see WARNINGS, PRECAUTIONS; Drug interactions]

• Reserve concomitant prescribing of Hydrocodone bitartrate and acetaminophen tablets and benzodiazepines or other CNS depressants for use in patients for whom alternative treatment options are inadequate.

• Limit dosages and durations to the minimum required.

• Follow patients for signs and symptoms of respiratory depression and sedation.

DESCRIPTION

Hydrocodone bitartrate and acetaminophen is supplied in tablet form for oral administration.
Hydrocodone bitartrate is an opioid analgesic and antitussive and occurs as fine, white crystals or as a crystalline powder. It is affected by light. The chemical name is: 4,5α-epoxy-3-methoxy-17-methylmorphinan-6-one tartrate (1:1) hydrate (2:5). It has the following structural formula:

Acetaminophen, 4’-hydroxyacetanilide, a slightly bitter, white, odorless, crystalline powder, is a non-opiate, non-salicylate analgesic and antipyretic. It has the following structural formula:

Hydrocodone bitartrate and acetaminophen tablets USP, for oral administration, are available in a variety of strengths as described in the following table.
Each hydrocodone bitartrate and acetaminophen tablet contains:

Strength | Hydrocodone Bitartrate | Acetaminophen
5 mg/325 mg 7.5 mg/325 mg 10 mg/325 mg | 5 mg 7.5 mg 10 mg | 325 mg 325 mg 325 mg

In addition each tablet contains the following inactive ingredients: colloidal silicon dioxide, croscarmellose sodium, crospovidone, magnesium stearate, microcrystalline cellulose, povidone, pregelatinized starch and stearic acid.
Meets USP Dissolution Test 1.

CLINICAL PHARMACOLOGY

Hydrocodone is a semisynthetic narcotic analgesic and antitussive with multiple actions qualitatively similar to those of codeine. Most of these involve the central nervous system and smooth muscle. The precise mechanism of action of hydrocodone and other opiates is not known, although it is believed to relate to the existence of opiate receptors in the central nervous system. In addition to analgesia, narcotics may produce drowsiness, changes in mood and mental clouding.
The analgesic action of acetaminophen involves peripheral influences, but the specific mechanism is as yet undetermined. Antipyretic activity is mediated through hypothalamic heat regulating centers. Acetaminophen inhibits prostaglandin synthetase. Therapeutic doses of acetaminophen have negligible effects on the cardiovascular or respiratory systems; however, toxic doses may cause circulatory failure and rapid, shallow breathing.
Pharmacokinetics
The behavior of the individual components is described below.
Hydrocodone
Following a 10 mg oral dose of hydrocodone administered to five adult male subjects, the mean peak concentration was 23.6 ± 5.2 ng/mL. Maximum serum levels were achieved at 1.3 ± 0.3 hours and the half-life was determined to be 3.8 ± 0.3 hours. Hydrocodone exhibits a complex pattern of metabolism including O-demethylation, N-demethylation and 6-keto reduction to the corresponding 6-α- and 6-β-hydroxy-metabolites. See OVERDOSAGE for toxicity information.
Acetaminophen
Acetaminophen is rapidly absorbed from the gastrointestinal tract and is distributed throughout most body tissues. The plasma half-life is 1.25 to 3 hours, but may be increased by liver damage and following overdosage. Elimination of acetaminophen is principally by liver metabolism (conjugation) and subsequent renal excretion of metabolites. Approximately 85% of an oral dose appears in the urine within 24 hours of administration, most as the glucuronide conjugate, with small amounts of other conjugates and unchanged drug. See OVERDOSAGE for toxicity information.

INDICATIONS AND USAGE

Hydrocodone bitartrate and acetaminophentablets are indicated for the management of relief of moderate to moderatelysevere pain, pain severe enough to require an opioid analgesic and for whichalternative treatments are inadequate.
Limitations of Use
Because of the risks of addiction, abuse, andmisuse, with opioids, even at recommended doses [see WARNINGS], reserve hydrocodonebitartrate and acetaminophen tablets for use in patients for whom alternativetreatment options [e.g., non-opioid analgesics]

- Have not been tolerated, or are not expected to be tolerated,
- Have not provided adequate analgesia, or are not expected to provide adequate analgesia

CONTRAINDICATIONS

Hydrocodonebitartrate and acetaminophen tablets are contraindicated in patients with:

- Significant respiratory depression [see WARNINGS]
- Acute or severe bronchial asthma in an unmonitored setting or in the absence of resuscitative equipment [see WARNINGS]
- Hypersensitivity to hydrocodone or acetaminophen
- Hypersensitive to other opioids which may exhibit cross-sensitivity to hydrocodone

WARNINGS

Addiction, Abuse, and Misuse

Hydrocodone bitartrate and acetaminophen tablet contains hydrocodone and acetaminophen a Schedule CII controlled substance. As an opioid, hydrocodone bitartrate andacetaminophen tablets exposes users to the risks of addiction, abuse, andmisuse [see DRUG ABUSE AND DEPENDENCE].

Although therisk of addiction in any individual is unknown, it can occur in patients appropriately prescribed hydrocodone bitartrate and acetaminophen tablets.Addiction can occur at recommended dosages and if the drug is misused orabused.

Assess eachpatient’s risk for opioid addiction, abuse, or misuse prior to prescribing hydrocodone bitartrate and acetaminophen tablets, and monitor all patients receiving hydrocodone bitartrate and acetaminophen tablets for the development of these behaviors or conditions. Risks are increased in patients with a personal or family historyof substance abuse (including drug or alcohol abuse or addiction) or mental illness (e.g., major depression). The potential for these risks should not, however, prevent the proper management of pain in any given patient. Patients at increased risk may be prescribed opioids such as hydrocodone bitartrate and acetaminophen tablets, but use in such patients necessitates intensive counseling about the risks andproperuse of hydrocodone bitartrate and acetaminophen tablets along with intensive monitoring for signs of addiction, abuse, and misuse.

Opioids are sought by drug abusers and people with addiction disorders and are subject to criminal diversion. Consider these risks when prescribing or dispensing hydrocodone bitartrate and acetaminophen tablets. Strategies to reduce these risks includeprescribing the drug in the smallest appropriate quantity and advising thepatient on the proper disposal of unused drug [see PRECAUTIONS; Information for Patients]. Contact local state professional licensing board or statecontrolled substances authority for information on how to prevent and detectabuse or diversion of this product.

Hepatotoxicity

Acetaminophenhas been associated with cases of acute liver failure, at times resulting inliver transplant and death. Most of the cases of liver injury are associated withthe use of acetaminophen at doses that exceed 4,000 milligrams per day, andoften involve more than one acetaminophen-containing product. The excessiveintake of acetaminophen may be intentional to cause self-harm or unintentionalas patients attempt to obtain more pain relief or unknowingly take otheracetaminophen-containing products.

The riskof acute liver failure is higher in individuals who ingest alcohol while taking acetaminophen. Instruct patients to look for acetaminophen or APAP on package labels and not to use more than one product that contains acetaminophen. Instruct patients to seek medical attention immediately upon ingestion of more than 4,000 milligrams of acetaminophen per day, even if they feel well.

Life-Threatening Respiratory Depression

Serious, life-threatening, or fatal respiratory depression has been reported with theuse of opioids, even when used as recommended. Respiratory depression, if notimmediately recognized and treated, may lead to respiratory arrest and death.Management of respiratory depression may include close observation, supportive measures, and use of opioid antagonists, depending on the patient’s clinical status [see OVERDOSAGE]. Carbon dioxide (CO2) retention from opioid-induced respiratory depression can exacerbate the sedating effects ofopioids.

While serious, life-threatening, or fatal respiratory depression can occur at anytime during the use of hydrocodone bitartrate and acetaminophen tablets, therisk is greatest during the initiation of therapy or following a dosageincrease. Monitor patients closely for respiratory depression, especiallywithin the first 24 to 72 hours of initiating therapy with and following dosage increases of hydrocodone bitartrate and acetaminophen tablets.

To reduce therisk of respiratory depression, proper dosing and titration of hydrocodonebitartrate and acetaminophen tablets are essential [see DOSAGE AND ADMINISTRATION]. Overestimating the hydrocodone bitartrate andacetaminophen tablets dosage when converting patients from another opioidproduct can result in a fatal overdose with the first dose.

Accidentalingestion of even one dose of hydrocodone bitartrate and acetaminophen tablets,especially by children, can result in respiratory depression and death due toan overdose of hydrocodoneand acetaminophen.

Neonatal Opioid Withdrawal Syndrome

Prolonged useof hydrocodone bitartrate and acetaminophen tablets during pregnancy can resultin withdrawal in the neonate. Neonatal opioid withdrawal syndrome, unlikeopioid withdrawal syndrome in adults, may be life-threatening if not recognizedand treated, and requires management according to protocols developed byneonatology experts. If opioid use is required for a prolonged period in apregnant woman, advise the patient of the risk of neonatal opioid withdrawalsyndrome and ensure that appropriate treatment will be available [seePRECAUTIONS;Information for Patients, Pregnancy].

Drug Interactions

Patientsreceiving other narcotic analgesics, antihistamines, antipsychotics, antianxietyagents, or other CNS depressants (including alcohol) concomitantly withhydrocodone bitartrate and acetaminophen tablets may exhibit an additive CNSdepression. When combined therapy is contemplated, the dose of one or bothagents should be reduced.
The use of MAO inhibitors or tricyclicantidepressants with hydrocodone preparations may increase the effect of eitherthe antidepressant or hydrocodone.

Drug/Laboratory Test Interactions

Acetaminophenmay produce false-positive test results for urinary 5-hydroxyindoleacetic acid.

Carcinogenesis, Mutagenesis, Impairment of Fertility

Noadequate studies have been conducted in animals to determine whetherhydrocodone or acetaminophen have a potential for carcinogenesis, mutagenesis,or impairment of fertility.

Pregnancy

Teratogenic Effects

PregnancyCategory C

Thereare no adequate and well-controlled studies in pregnant women. Hydrocodone bitartrate and acetaminophen tablets should be used during pregnancy only ifthe potential benefit justifies the potential risk to the fetus.

Nonteratogenic Effects

Babies born to mothers who have been taking opioids regularly prior to delivery will be physically dependent. The withdrawal signs include irritability and excessive crying, tremors, hyperactive reflexes, increased respiratory rate, increased stools, sneezing, yawning, vomiting, and fever. The intensity of the syndrome does not always correlate with the duration of maternal opioid use ordose. There is no consensus on the best method of managing withdrawal.

Labor and Delivery

Aswith all narcotics, administration of this product to the mother shortly beforedelivery may result in some degree of respiratory depression in the newborn,especially if higher doses are used.

Nursing Mothers

Acetaminophenis excreted in breast milk in small amounts, but the significance of itseffects on nursing infants is not known. It is not known whether hydrocodone isexcreted in human milk. Because many drugs are excreted in human milk andbecause of the potential for serious adverse reactions in nursing infants fromhydrocodone and acetaminophen, a decision should be made whether to discontinuenursing or to discontinue the drug, taking into account the importance of thedrug to the mother.

Pediatric Use

Safetyand effectiveness in the pediatric population have not been established.

Geriatric Use

Clinicalstudies of hydrocodone bitartrate 5 mg and acetaminophen 500 mg did not includesufficient numbers of subjects aged 65 and over to determine whether theyrespond differently from younger subjects. Other reported clinical experiencehas not identified differences in responses between the elderly and youngerpatients. In general, dose selection for an elderly patient should be cautious,usually starting at the low end of the dosing range, reflecting the greaterfrequency of decreased hepatic, renal, or cardiac function, and of concomitantdisease or other drug therapy.

Hydrocodoneand the major metabolites of acetaminophen are known to be substantiallyexcreted by the kidney. Thus the risk of toxic reactions may be greater inpatients with impaired renal function due to the accumulation of the parentcompound and/or metabolites in the plasma. Because elderly patients are morelikely to have decreased renal function, care should be taken in doseselection, and it may be useful to monitor renal function.

Hydrocodonemay cause confusion and over-sedation in the elderly; elderly patientsgenerally should be started on low doses of hydrocodone bitartrate andacetaminophen tablets and observed closely.

Risks from Concomitant Use with Benzodiazepines or Other CNS Depressants

Profound sedation, respiratory depression, coma, and death may result from the concomitant use of Hydrocodone bitartrate and acetaminophen tablets with benzodiazepines or other CNS depressants (e.g., non-benzodiazepine sedatives/hypnotics, anxiolytics,tranquilizers, muscle relaxants, general anesthetics, antipsychotics, other opioids, alcohol). Because of these risks, reserve concomitant prescribing of these drugs for use in patients for whom alternative treatment options are inadequate.

Observational studies have demonstrated that concomitant use of opioid analgesics and benzodiazepines increases the risk of drug-related mortality compared to use of opioid analgesics alone. Because of similar pharmacological properties, it is reasonable to expect similar risk with the concomitant use of other CNS depressant drugs with opioid analgesics [see PRECAUTIONS; Drug Interactions].

If the decision is made to prescribe a benzodiazepine or other CNS depressant concomitantly with an opioid analgesic, prescribe the lowest effective dosages and minimum durations of concomitant use. In patients already receiving an opioid analgesic, prescribe a lower initial dose of the benzodiazepine or other CNS depressant than indicated in the absence of an opioid, and titrate based on clinical response. If an opioid analgesic is initiated in a patient already taking a benzodiazepine or other CNS depressant, prescribe a lower initial dose of the opioid analgesic, and titrate based on clinical response. Follow patients closely for signs and symptoms of respiratory depression and sedation.

Advise both patients and caregivers about the risks of respiratory depression and sedation when Hydrocodone bitartrate and acetaminophen tablet is used with benzodiazepines or other CNS depressants (including alcohol and illicit drugs). Advice patients not to drive or operate heavy machinery until the effects of concomitant use of the benzodiazepine or other CNS depressant have been determined. Screen patients for risk of substance use disorders, including opioid abuse and misuse, and warn them of the risk for overdose and death associated with the use of additional CNS depressants including alcohol and illicit drugs [seePRECAUTIONS; Drug Interactions) and PRECAUTIONS; Information for Patients ].

Life-Threatening Respiratory Depression in Patients with Chronic Pulmonary Disease or in Elderly, Cachectic, or Debilitated Patients

The use of hydrocodone bitartrate and acetaminophen tablets in patients with acute or severe bronchial asthma in an unmonitored setting or in the absence of resuscitative equipmentis contraindicated.

Patientswith Chronic Pulmonary Disease: Hydrocodonebitartrate and acetaminophen tablets-treated patients with significant chronicobstructive pulmonary disease or cor pulmonale, and those with a substantiallydecreased respiratory reserve, hypoxia, hypercapnia, or pre-existingrespiratory depression are at increased risk of decreased respiratory driveincluding apnea, even at recommended dosages of hydrocodone bitartrate andacetaminophen tablets [see WARNINGS].

Elderly,Cachetic, or Debilitated Patients: Life-threateningrespiratory depression is more likely to occur in elderly, cachectic, ordebilitated patients because they may have altered pharmacokinetics or alteredclearance compared to younger, healthier patients [see WARNINGS].

Monitor suchpatients closely, particularly when initiating and titrating hydrocodonebitartrate and acetaminophen tablets and when hydrocodone bitartrate andacetaminophen tablets is given concomitantly with other drugs that depressrespiration [see WARNINGS].Alternatively, consider the use ofnon-opioid analgesics in these patients.

Adrenal Insufficiency

Cases of adrenal insufficiency have beenreported with opioid use, more often following greater than 1 month of use.Presentation of adrenal insufficiency may include non-specific symptoms andsigns including nausea, vomiting, anorexia, fatigue, weakness, dizziness, andlow blood pressure. If adrenal insufficiency is suspected, confirm thediagnosis with diagnostic testing as soon as possible. If adrenal insufficiencyis diagnosed, treat with physiologic replacement doses of corticosteroids. Weanthe patient off of the opioid to allow adrenal function to recover and continuecorticosteroid treatment until adrenal function recovers. Other opioids may betried as some cases reported use of a different opioid without recurrence ofadrenal insufficiency. The information available does not identify anyparticular opioids as being more likely to be associated with adrenal insufficiency.

PRECAUTIONS

General
Special Risk Patients

As with any narcotic analgesic agent, hydrocodonebitartrate and acetaminophen tablets should be used with caution in elderly ordebilitated patients and those with severe impairment of hepatic or renalfunction, hypothyroidism, Addison’s disease, prostatic hypertrophy or urethralstricture. The usual precautions should be observed and the possibility of respiratorydepression should be kept in mind.

Cough Reflex

Hydrocodone suppresses the cough reflex;as with all narcotics, caution should be exercised when hydrocodone bitartrateand acetaminophen tablets are used postoperatively and in patients with pulmonarydisease.

Information for Patients/Caregivers

Addiction, Abuse, and Misuse

Informpatients that the use of hydrocodone bitartrate and acetaminophen tablets, even when taken as recommended, can result in addiction, abuse, and misuse, which can lead to overdose and death [see WARNINGS]. Instruct patients not to share hydrocodone bitartrate and acetaminophen tablets with others and to take steps to protect hydrocodone bitartrate and acetaminophen tablets from theft ormisuse.

Life-Threatening Respiratory Depression

Informpatients of the risk of life-threatening respiratory depression, including information that the risk is greatest when starting hydrocodone bitartrate andacetaminophen tablets or when the dosage is increased, and that it can occureven at recommended dosages [see WARNINGS]. Advise patients how to recognize respiratory depression and to seek medical attention if breathing difficulties develop.

Accidental Ingestion

Inform patients that accidental ingestion, especially by children, may result inrespiratory depression or death [see WARNINGS]. Instruct patients totake steps to store hydrocodone bitartrate and acetaminophen tablets securely.Opioids are sought by drug abusers and people with addiction disorders and aresubject to criminal diversion. Consider these risks when prescribing ordispensing hydrocodone bitartrate and acetaminophen tablets. Strategies toreduce these risks include prescribing the drug in the smallest appropriatequantity and advising the patient on the proper disposal of unused drug [see PRECAUTIONS; Information for Patients]. Contact local state professional licensing boardor state controlled substances authority for information on how to prevent anddetect abuse or diversion of this product.

Interactions with Benzodiazepines and Other CNS Depressants

Inform patients and caregivers that potentially fatal additive effects may occur if Hydrocodone bitartrate and acetaminophen tablets is used with benzodiazepines or other CNS depressants, including alcohol, and not to use these concomitantly unless supervised by a health care provider [see WARNINGS and PRECAUTIONS; Drug Interactions].

Serotonin Syndrome

Inform patients that hydrocodone bitartrate and acetaminophen tablets could cause a rare but potentially life-threatening condition resulting from concomitant administration of serotonergic drugs. Warn patients of the symptoms ofserotonin syndrome and to seek medical attention right away if symptoms develop. Instruct patients to inform their physicians if they are taking, orplan to take serotonergic medications [see PRECAUTIONS; Error! Hyperlink reference not valid.].

Adrenal Insufficiency

Inform patients that hydrocodone bitartrate and acetaminophen tablets could cause adrenal insufficiency, a potentially life-threatening condition. Adrenal insufficiency may present with non-specific symptoms and signs such as nausea,vomiting, anorexia, fatigue, weakness, dizziness, and low blood pressure.Advise patients to seek medical attention if they experience a constellation ofthese symptoms [seeWARNINGS].

Pregnancy

Neonatal Opioid Withdrawal Syndrome

Inform patients that prolonged use of hydrocodone bitartrate and acetaminophen tablets during pregnancy can result in neonatal opioid withdrawal syndrome, which maybe life-threatening if not recognized and treated [see WARNINGS, PRECAUTIONS;Error! Hyperlink reference not valid.] Embryo-Fetal Toxicity

Inform female patients of reproductive potential that hydrocodone bitartrate andacetaminophen can cause fetal harm and to inform the prescriber of a known orsuspected pregnancy [see PRECAUTIONS; Error! Hyperlink reference not valid.].

Lactation

Advise nursing mothers to monitor infants for increased sleepiness (more than usual), breathing difficulties, or limpness. Instruct nursing mothers to seek immediate medical care if they notice these signs [see PRECAUTIONS; Error! Hyperlink reference not valid.].

Disposal of Unused Hydrocodone Bitartrate and Acetaminophen Tablets

Advise patients on the proper disposal of unused drug [see PRECAUTIONS; Information for Patients/Caregivers] by contacting local state professional licensing board orstate controlled substances authority for information on how to prevent anddetect abuse or diversion of this product.

Drug Interactions

Patients receiving other narcotic analgesics, antihistamines, antipsychotics, antianxiety agents, or other CNS depressants (including alcohol) concomitantlywith hydrocodone bitartrate and acetaminophen tablets may exhibit an additiveCNS depression. When combined therapy is contemplated, the dose of one or bothagents should be reduced.
The use of MAO inhibitors or tricyclic antidepressants with hydrocodone preparations may increase the effect of either the antidepressant or hydrocodone.

Hydrocodone bitartrate and acetaminophen tablets contains hydrocodone and acetaminophen, asubstance with a high potential for abuse similar to other opioids including withdrawal also may be precipitated through the administration of drugs with opioid antagonist activity (e.g., naloxone, nalmefene), mixedagonist/antagonist analgesics (pentazocine, butorphanol, nalbuphine), orpartial agonists (buprenorphine). Physical dependence may not occur to aclinically significant degree until after several days to weeks of continuedopioid usage. Hydrocodone bitartrate and acetaminophen tablets can be abusedand is subject to misuse, addiction, and criminal diversion [seeWARNINGS].

Benzodiazepines and other Central Nervous System (CNS) Depressants

Due to additive pharmacologic effect, the concomitant use of benzodiazepines or other CNS depressants such as alcohol, other sedatives/hypnotics, anxiolytics, tranquilizers, muscle relaxants, general anesthetics, antipsychotics, and other opioids, can increases the risk of respiratory depression, profound sedation, coma, and death. Reserve concomitant prescribing of these drugs for use in patients for whom alternative treatment options are inadequate. Limit dosages and durations to the minimum required. Follow patients closely for signs of respiratory depression and sedation [see WARNINGS].

Serotonergic Drugs

The concomitantuse of opioids with other drugs that affect the serotonergic neurotransmitter system, such as selective serotonin reuptake inhibitors (SSRIs), serotonin andnorepinephrine reuptake inhibitors (SNRIs), tricyclic antidepressants (TCAs),triptans, 5-HT3 receptor antagonists, drugs that effect theserotonin neurotransmitter system (e.g., mirtazapine, trazodone, tramadol), andmonoamine oxidase (MAO) inhibitors (those intended to treat psychiatricdisorders and also others, such as linezolid and intravenous methylene blue),has resulted in serotonin syndrome [see PRECAUTIONS; Information for Patients/Caregivers].

If concomitant use is warranted, carefully observe the patient, particularly during treatment initiation and dose adjustment. Discontinue hydrocodone bitartrateand acetaminophen tablets if serotonin syndrome is suspected.

Carcinogenesis, Mutagenesis, Impairment of Fertility

Infertility

Chronic useof opioids may cause reduced fertility in females and males of reproductivepotential. It is not known whether these effects on fertility are reversible[see ADVERSE REACTIONS].

Pregnancy

Fetal/Neonatal Adverse Reactions

Prolonged useof opioid analgesics during pregnancy for medical or nonmedical purposes canresult in physical dependence in the neonate and neonatal opioid withdrawalsyndrome shortly after birth.

Neonatal opioid withdrawal syndrome presents as irritability, hyperactivity and abnormalsleep pattern, high pitched cry, tremor, vomiting, diarrhea and failure to gainweight. The onset, duration, and severity of neonatal opioid withdrawalsyndrome vary based on the specific opioid used, duration of use, timing andamount of last maternal use, and rate of elimination of the drug by thenewborn. Observe newborns for symptoms of neonatal opioid withdrawal syndromeand manage accordingly [see WARNINGS].
Labor or Delivery

Opioids cross the placenta and may produce respiratory depression and psycho-physiologic effects in neonates. An opioid antagonist, such as naloxone, must be availablefor reversal of opioid-induced respiratory depression in the neonate. Hydrocodone bitartrate and acetaminophen tablets is not recommended for use inpregnant women during or immediately prior to labor, when other analgesic techniques are more appropriate. Opioid analgesics, including hydrocodonebitartrate and acetaminophen, can prolong labor through actions which temporarily reduce the strength, duration, and frequency of uterine contractions. However, this effect is not consistent and may be offset by anincreased rate of cervical dilation, which tends to shorten labor. Monitorneonates exposed to opioid analgesics during labor for signs of excess sedationand respiratory depression.

Nursing Mothers

The developmental and health benefits of breastfeeding should be considered alongwith the mother’s clinical need for hydrocodone bitartrate and acetaminophen and any potential adverse effects on the breastfed infant from hydrocodone bitartrate and acetaminophen tablets or from the underlying maternal condition.Infants exposed to hydrocodone bitartrate and acetaminophen through breast milkshould be monitored for excess sedation and respiratory depression. Withdrawal symptoms can occur in breastfed infants when maternal administration of anopioid analgesic is stopped, or when breast-feeding is stopped.

Geriatric Use

Elderly patients (aged 65 years or older) may have increased sensitivity to hydrocodone bitartrate and acetaminophen tablets. In general, use caution when selecting adosage for an elderly patient, usually starting at the low end of the dosing range, reflecting the greater frequency of decreased hepatic, renal, or cardiac function and of concomitant disease or other drug therapy. Respiratory depression is the chief risk for elderly patients treated with opioids, and hasoccurred after large initial doses were administered to patients who were not opioid-tolerant or when opioids were co-administered with other agents that depress respiration. Titrate the dosage of hydrocodone bitartrate andacetaminophen tablets slowly in geriatric patients [see WARNINGS].

ADVERSE REACTIONS

The most frequently reported adverse reactions include: lightheadedness, dizziness, sedation, nausea and vomiting. These effects seem to be more prominent in ambulatory than in nonambulatory patients and some of these adverse reactions may be alleviated if the patient lies down.
Other adverse reactions include
Central Nervous System
Drowsiness, mental clouding, lethargy, impairment of mental and physical performance, anxiety, fear, dysphoria, psychic dependence, mood changes.
Gastrointestinal System
Prolonged administration of hydrocodone bitartrate and acetaminophen tablets may produce constipation.
Genitourinary System
Ureteral spasm, spasm of vesical sphincters and urinary retention have been reported with opiates.
Respiratory Depression
Hydrocodone bitartrate may produce dose-related respiratory depression by acting directly on the brain stem respiratory center. (see OVERDOSAGE).
Special Senses
Cases of hearing impairment or permanent loss have been reported predominantly in patients with chronic overdose.
Dermatological
Skin rash, pruritus.
The following adverse drug events may be borne in mind as potential effects of acetaminophen: allergic reactions, rash, thrombocytopenia, agranulocytosis.
Potential effects of high dosage are listed in the OVERDOSAGE section.

Postmarketing Experience

- serotonin syndrome
- adrenal insufficiency

Androgen Deficiency

Chronic useof opioids may influence the hypothalamic-pituitary-gonadal axis, leading toandrogen deficiency that may manifest as symptoms of hypogonadism, such asimpotence, erectile dysfunction, or amenorrhea. The causal role of opioids inthe syndrome of hypogonadism is unknown because the various medical, physical, lifestyle, and psychological stressors that may influence gonadal hormone levels have not been adequately controlled for in studies conducted to date. Patients presenting with symptoms of androgen deficiency should undergo laboratory evaluation.

DRUG ABUSE AND DEPENDENCE

Controlled Substance

Hydrocodone bitartrate and acetaminophen tablets contains hydrocodone and acetaminophen, aSchedule CII controlled substance.

Abuse

Hydrocodone bitartrate and acetaminophen tablets contains hydrocodone and acetaminophen, asubstance with a high potential for abuse similar to other opioids including withdrawal also may be precipitated through the administration of drugs withopioid antagonist activity (e.g., naloxone, nalmefene), mixedagonist/antagonist analgesics (pentazocine, butorphanol, nalbuphine), orpartial agonists (buprenorphine). Physical dependence may not occur to aclinically significant degree until after several days to weeks of continuedopioid usage. Hydrocodone bitartrate and acetaminophen tablets can be abusedand is subject to misuse, addiction, and criminal diversion [see WARNINGS].

All patients treated with opioids require careful monitoring for signs of abuse and addiction, since use of opioid analgesic products carries the risk of addiction even under appropriate medical use.

Prescription drug abuse is the intentional non-therapeutic use of a prescription drug, evenonce, for its rewarding psychological or physiological effects.

Drug addiction is a cluster of behavioral, cognitive, and physiological phenomenathat develop after repeated substance use and includes: a strong desire to take the drug, difficulties in controlling its use, persisting in its use despite harmful consequences, a higher priority given to drug use than to other activities and obligations, increased tolerance, and sometimes a physical withdrawal.

“Drug-seeking”behavior is very common in persons with substance use disorders. Drug-seeking tactics include emergency calls or visits near the end of office hours, refusal to undergo appropriate examination, testing, or referral, repeated “loss” of prescriptions, tampering with prescriptions and reluctance to provide priormedical records or contact information for other treating health careprovider(s). “Doctor shopping” (visiting multiple prescribers) to obtainadditional prescriptions is common among drug abusers and people suffering from untreated addiction. Preoccupation with achieving adequate pain relief can beappropriate behavior in a patient with poor pain control.

Abuse and addiction are separate and distinct from physical dependence and tolerance.Health care providers should be aware that addiction may not be accompanied by concurrent tolerance and symptoms of physical dependence in all addicts. Inaddition, abuse of opioids can occur in the absence of true addiction.

Hydrocodone bitartrate and acetaminophen tablets, like other opioids, can be diverted fornon-medical use into illicit channels of distribution. Careful record-keepingof prescribing information, including quantity, frequency, and renewalrequests, as required by state and federal law, is strongly advised. Properassessment of the patient, proper prescribing practices, periodic re-evaluationof therapy, and proper dispensing and storage are appropriate measures thathelp to limit abuse of opioid drugs.

Risks Specific to Abuse of Hydrocodone Bitartrate and Acetaminophen Tablets

Hydrocodone

Serious overdose with hydrocodone is characterized by respiratory depression (adecrease in respiratory rate and/or tidal volume, Cheyne-Stokes respiration,cyanosis), extreme somnolence progressing to stupor or coma, skeletal muscleflaccidity, cold and clammy skin, and sometimes bradycardia and hypotension. Insevere overdosage, apnea, circulatory collapse, cardiac arrest and death mayoccur.

Acetaminophen

In acetaminophen overdosage: dose-dependent, potentially fatal hepatic necrosis isthe most serious adverse effect. Renal tubular necrosis, hypoglycemic coma, andcoagulation defects may also occur.

Early symptoms following a potentially hepatotoxic overdose may include: nausea,vomiting, diaphoresis and general malaise. Clinical and laboratory evidence ofhepatic toxicity may not be apparent until 48 to 72 hours post-ingestion.

Treatment

A single or multiple drug overdose with hydrocodone and acetaminophen is a potentially lethal polydrug overdose, and consultation with a regional poison control center is recommended. Immediate treatment includes support of cardiorespiratory function and measures to reduce drug absorption. Oxygen, intravenous fluids, vasopressors, and other supportive measures should beemployed as indicated. Assisted or controlled ventilation should also beconsidered.

For hydrocodone overdose, primary attention should be given to the reestablishment of adequate respiratory exchange through provision of a patent airway and the institution of assisted or controlled ventilation. The narcotic antagonistnaloxone hydrochloride is a specific antidote against respiratory depressionwhich may result from overdosage or unusual sensitivity to narcotics, includinghydrocodone. Since the duration of action of hydrocodone may exceed that of theantagonist, the patient should be kept under continued surveillance, andrepeated doses of the antagonist should be administered as needed to maintainadequate respiration. A narcotic antagonist should not be administered in theabsence of clinically significant respiratory or cardiovascular depression.

Gastricdecontamination with activated charcoal should be administered just prior toN-acetylcysteine (NAC) to decrease systemic absorption if acetaminophen isknown or suspected to have occurred within a few hours of presentation. Serumacetaminophen levels should be obtained immediately if the patient presents 4hours or more after ingestion to assess potential risk of hepatotoxicity;acetaminophen levels drawn less than 4 hours post-ingestion may be misleading.To obtain the best possible outcome, NAC should be administered as soon aspossible where impending or evolving liver injury is suspected. Intravenous NACmay be administered when circumstances preclude oral administration.

Vigoroussupportive therapy is required in severe intoxication. Procedures to limit thecontinuing absorption of the drug must be readily performed since the hepaticinjury is dose-dependent and occurs early in the course of intoxication.

Dependence

Bothtolerance and physical dependence can develop during chronic opioid therapy.Tolerance is the need for increasing doses of opioids to maintain a definedeffect such as analgesia (in the absence of disease progression or otherexternal factors). Tolerance may occur to both the desired and undesiredeffects of drugs, and may develop at different rates for different effects.Physical dependence results in withdrawal symptoms after abrupt discontinuationor a significant dosage reduction of a drug. Withdrawal also may beprecipitated through the administration of drugs with opioid antagonistactivity (e.g., naloxone, nalmefene), mixed agonist/antagonist analgesics(pentazocine, butorphanol, nalbuphine), or partial agonists (buprenorphine).Physical dependence may not occur to a clinically significant degree untilafter several days to weeks of continued opioid usage.

Hydrocodonebitartrate and acetaminophen tablets should not be abruptly discontinued [see DOSAGE AND ADMINISTRATION]. If hydrocodone bitartrate and acetaminophentablets is abruptly discontinued in a physically dependent patient, awithdrawal syndrome may occur. Some or all of the following can characterizethis syndrome: restlessness, lacrimation, rhinorrhea, yawning, perspiration,chills, myalgia, and mydriasis. Other signs and symptoms also may develop,including: irritability, anxiety, backache, joint pain, weakness, abdominalcramps, insomnia, nausea, anorexia, vomiting, diarrhea, or increased bloodpressure, respiratory rate, or heart rate.

Infants bornto mothers physically dependent on opioids will also be physically dependentand may exhibit respiratory difficulties and withdrawal signs [see PRECAUTIONS;Error! Hyperlink reference not valid.].

OVERDOSAGE

Clinical Presentation

Acuteoverdose with hydrocodone bitartrate and acetaminophen tablets can bemanifested by respiratory depression, somnolence progressing to stupor or coma,skeletal muscle flaccidity, cold and clammy skin, constricted pupils, and, insome cases, pulmonary edema, bradycardia, hypotension, partial or completeairway obstruction, atypical snoring, and death. Marked mydriasis rather thanmiosis may be seen with hypoxia in overdose situations.

Treatment of Overdose

In case ofoverdose, priorities are the reestablishment of a patent and protected airwayand institution of assisted or controlled ventilation, if needed. Employ othersupportive measures (including oxygen and vasopressors) in the management ofcirculatory shock and pulmonary edema as indicated. Cardiac arrest orarrhythmias will require advanced life-support techniques.

The opioidantagonists, naloxone or nalmefene, are specific antidotes to respiratorydepression resulting from opioid overdose. For clinically significantrespiratory or circulatory depression secondary to hydrocodone bitartrate andacetaminophen tablets overdose, administer an opioid antagonist. Opioidantagonists should not be administered in the absence of clinically significantrespiratory or circulatory depression secondary to hydrocodone bitartrate andacetaminophen tablets overdose.

Because theduration of opioid reversal is expected to be less than the duration of actionof hydrocodone bitartrate and acetaminophen tablets in hydrocodone bitartrateand acetaminophen tablets, carefully monitor the patient until spontaneousrespiration is reliably re-established. If the response to an opioid antagonistis suboptimal or only brief in nature, administer additional antagonist asdirected by the product’s prescribing information.

In anindividual physically dependent on opioids, administration of the recommendedusual dosage of the antagonist will precipitate an acute withdrawal syndrome.The severity of the withdrawal symptoms experienced will depend on the degreeof physical dependence and the dose of the antagonist administered. If adecision is made to treat serious respiratory depression in the physicallydependent patient, administration of the antagonist should be begun with careand by titration with smaller than usual doses of the antagonist.

DOSAGE AND ADMINISTRATION

Important Dosage and Administration Instructions

Initiate thedosing regimen for each patient individually, taking into account the patient'sseverity of pain, patient response, prior analgesic treatment experience, andrisk factors for addiction, abuse, and misuse [see WARNINGS].

Monitorpatients closely for respiratory depression, especially within the first 24 to 72hours of initiating therapy and following dosage increases with hydrocodonebitartrate and acetaminophen tablets and adjust the dosage accordingly [see WARNINGS].

Dosage should be adjusted according tothe severity of the pain and the response of the patient. However, it should bekept in mind that tolerance to hydrocodone can develop with continued use andthat the incidence of untoward effects is dose related.

Initial Dosage Treatment with Hydrocodone Bitartrate and Acetaminophen Tablets

The usual adult dosageis one tablet every four to six hours as needed for pain. The total dailydosage should not exceed 6 tablets.

5 mg/325 mg | The usual adult dosage is one or two tablets every four to six hours as needed for pain.
7.5 mg/325 mg | The usual adult dosage is one tablet every four to six hours as needed for pain. The total daily dosage should not exceed 6 tablets.
10 mg/325 mg | The usual adult dosage is one tablet every four to six hours as needed for pain. The total daily dosage should not exceed 6 tablets.

Titrationand Maintenance of Therapy

Individually titrate hydrocodonebitartrate and acetaminophen tablets to a dose that provides adequate analgesiaand minimizes adverse reactions. Continually reevaluate patients receiving hydrocodonebitartrate and acetaminophen tablets to assess the maintenance of pain controland the relative incidence of adverse reactions, as well as monitoring for thedevelopment of addiction, abuse, or misuse [see WARNINGS]. Frequentcommunication is important among the prescriber, other members of thehealthcare team, the patient, and the caregiver/family during periods ofchanging analgesic requirements, including initial titration.

If the levelof pain increases after dosage stabilization, attempt to identify the source ofincreased pain before increasing the hydrocodone bitartrate and acetaminophentablets dosage. If unacceptable opioid-related adverse reactions are observed,consider reducing the dosage. Adjust the dosage to obtain an appropriatebalance between management of pain and opioid-related adverse reactions.

Discontinuation of Hydrocodone Bitartrate and Acetaminophen Tablets

When apatient who has been taking hydrocodone bitartrate and acetaminophen tabletsregularly and may be physically dependent no longer requires therapy with hydrocodonebitartrate and acetaminophen tablets, use a gradual downward titration of thedosage to prevent signs and symptoms of withdrawal. Do not stop hydrocodonebitartrate and acetaminophen tablets abruptly [see WARNINGS, DRUG ABUSE ANDDEPENDENCE].

HOW SUPPLIED

Hydrocodone Bitartrate and Acetaminophen Tablets USP are available in the following strengths:
Hydrocodone Bitartrate and Acetaminophen Tablet USP, 10 mg/325 mg is available as white to off-white, oval shaped tablets, debossed with “U03” on one side and break-line on the other side. Each tablet contains 10 mg hydrocodone bitartrate and 325 mg acetaminophen.
Bottles of 12 NDC 63187-778-12
Bottles of 15 NDC 63187-778-15

Bottles of 20 NDC 63187-778-20
Bottles of 30 NDC 63187-778-30

Bottles of 60 NDC 63187-778-60
Bottles of 90 NDC 63187-778-90

Storage: Store at 20° to 25°C (68° to 77°F). [See USP Controlled Room Temperature.]
Dispense in a tight, light-resistant container as defined in the USP with a child-resistant closure. Keep this and all medication out of the reach of children.
A Schedule C-II controlled drug substance.
Dispense with Medication Guide available at www.aurobindousa.com/product-medication-guides
Manufactured by:
Aurolife Pharma LLC
Dayton, NJ 08810
Manufactured for:
Aurobindo Pharma USA, Inc.
Dayton, NJ 08810

Repackaged by:
Proficient Rx LP.
Thousand Oaks, CA 91320
Revised: 09/2016

MEDICATION GUIDE

Hydrocodone Bitartrate and Acetaminophen Tablets, USP CII

HIGH-droe-KOE-dohnby-TAR-trate/ass-eet-ah-MEE-noe-fen

Hydrocodone Bitartrate and Acetaminophen Tablets are:

- A strong prescription pain medicine that contains an opioid (narcotic) that is used for the management of relief of moderate to moderately severe pain, pain severe enough to require an opioid analgesic and for which alternative treatments are inadequate or when non-opioid pain medicines do not treat your pain well enough or you cannot tolerate them.
- An opioid pain medicine that can put you at risk for overdose and death. Even if you take your dose correctly as prescribed you are at risk for opioid addiction, abuse, and misuse that can lead to death.

Important information about Hydrocodone Bitartrate and Acetaminophen Tablets:

- Get emergency help right away if you take too much hydrocodone bitartrate and acetaminophen tablets (overdose). When you first start taking hydrocodone bitartrate and acetaminophen tablets, when your dose is changed, or if you take too much (overdose), serious or life-threatening breathing problems that can lead to death may occur.
- Taking hydrocodone bitartrate and acetaminophen tablets with other opioid medicines,benzodiazepines, alcohol, or other central nervous system depressants (including street drugs) can cause severe drowsiness, decreased awareness, breathing problems, coma and death.
- Never give anyone else your hydrocodone bitartrate and acetaminophen tablets. They could die from taking it. Store hydrocodone bitartrate and acetaminophen tablets away from children and in a safe place to prevent stealing or abuse. Selling or giving away hydrocodone bitartrate and acetaminophen tablets is against the law.

Do not take Hydrocodone Bitartrate and Acetaminophen Tablets if you have:

- acute or severe bronchial asthma, trouble breathing, or other lung problems.
- a bowel blockage or have narrowing of the stomach or intestines.
- significant respiratory depression
- severe impairment of hepatic or renal function, hypothyroidism, Addison’s disease, prostatic hypertrophy or urethral stricture

Before taking Hydrocodone Bitartrate and Acetaminophen Tablets, tell your healthcareprovider if you have a history of:
• head injury, seizures
• liver, kidney, thyroid problems
• problems urinating
• pancreas or gallbladder problems
• abuse of street or prescription drugs, alcohol addiction, or mental health problems.

Tell your healthcare provider if you are:

- pregnant or planning to become pregnant. Prolonged use of hydrocodone bitartrate and acetaminophen tablets during pregnancy can cause withdrawal symptoms in your newborn baby that could be life-threatening if not recognized and treated.
- breastfeeding. Hydrocodone bitartrate and acetaminophen tablets passes into breast milk and may harm your baby.
- taking prescription or over-the-counter medicines, vitamins, or herbal supplements. Taking hydrocodone bitartrate and acetaminophen tablets with certain other medicines can cause serious side effects that could lead to death.

Whentaking Hydrocodone Bitartrate and Acetaminophen Tablets:

- Do not change your dose. Take hydrocodone bitartrate and acetaminophen tablets exactly as prescribed by your healthcare provider.
- The usual adult dosage is one tablet every four to six hours as needed for pain. The total daily dosage should not exceed 6 tablets. Do not take more than your prescribed dose. If you miss a dose, take your next dose at your usual time.
- Call your healthcare provider if the dose you are taking does not control your pain.
- If you have been taking hydrocodone bitartrate and acetaminophen tablets regularly, do not stop taking hydrocodone bitartrate and acetaminophen tablets without talking to your healthcare provider.
- After you stop taking hydrocodone bitartrate and acetaminophen tablets, contact local state professional licensing board or state controlled substances authority for information on how to prevent and detect abuse or diversion of this product.

While taking Hydrocodone Bitartrate and Acetaminophen Tablets DO NOT:

- Drive or operate heavy machinery, until you know how hydrocodone bitartrate and acetaminophen tablets affects you. Hydrocodone bitartrate and acetaminophen tablets can make you sleepy, dizzy, or lightheaded.
- Drink alcohol or use prescription or over-the-counter medicines that contain alcohol. Using products containing alcohol during treatment with hydrocodone bitartrate and acetaminophen tablets may cause you to overdose and die.

The possible side effects of hydrocodone Bitartrate and Acetaminophen Tablets:

- constipation, nausea, sleepiness, vomiting, tiredness, headache, dizziness, abdominal pain. Call your healthcare provider if you have any of these symptoms and they are severe.

Get emergency medical help if you have:

- trouble breathing, shortness of breath, fast heartbeat, chest pain, swelling of your face, tongue, or throat, extreme drowsiness, light-headedness when changing positions, feeling faint, agitation, high body temperature, trouble walking, stiff muscles, or mental changes such as confusion.

General Information about Hydrocodone Bitartrate and Acetaminophen Tablets

Medicinesare sometimes prescribed for purposes other than those listed in a MedicationGuide. Do not use hydrocodonebitartrate and acetaminophen tablets for a conditionfor which it was not prescribed. Do not give hydrocodone bitartrate andacetaminophen tablets to other people even if theyhave the same condition, they may harm them.

These are notall the possible side effects of hydrocodone bitartrate and acetaminophentablets. Call your doctor for medical advice about side effects. You may alsorequest medical information or to report suspected adverse reactions, contactAurobindo Pharma USA, Inc. at 1-866-850-2876 or FDA at 1-800-FDA-1088. Formore information go to dailymed.nlm.nih.gov

What are the ingredients in Hydrocodone Bitartrate andAcetaminophen Tablets?

Active Ingredients: hydrocodone bitartrate and acetaminophen

Inactive ingredients: colloidal silicon dioxide, croscarmellose sodium,crospovidone, magnesium stearate, microcrystalline cellulose, povidone,pregelatinized starch and stearic acid.

ThisMedication Guide has been approved by the U.S. Food and Drug Administration.

Manufacturedby:
AurolifePharma LLC
Dayton, NJ08810
Manufacturedfor:
AurobindoPharma USA, Inc.
Dayton, NJ 08810

Repackaged by:
Proficient Rx LP.
Thousand Oaks, CA 91320
Revised:09/2016

PACKAGE LABEL-PRINCIPAL DISPLAY PANEL - 10 mg/325 mg (30 Tablet Bottle)

NDC 63187-778-30
Hydrocodone Bitartrate and
Acetaminophen Tablets, USP CII
10 mg/325 mg
Rx only 30 Tablets